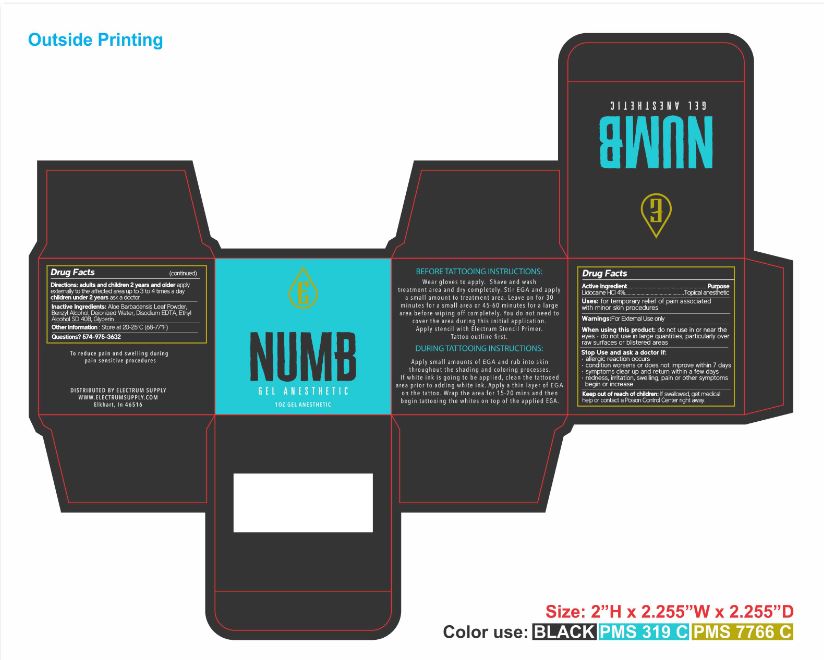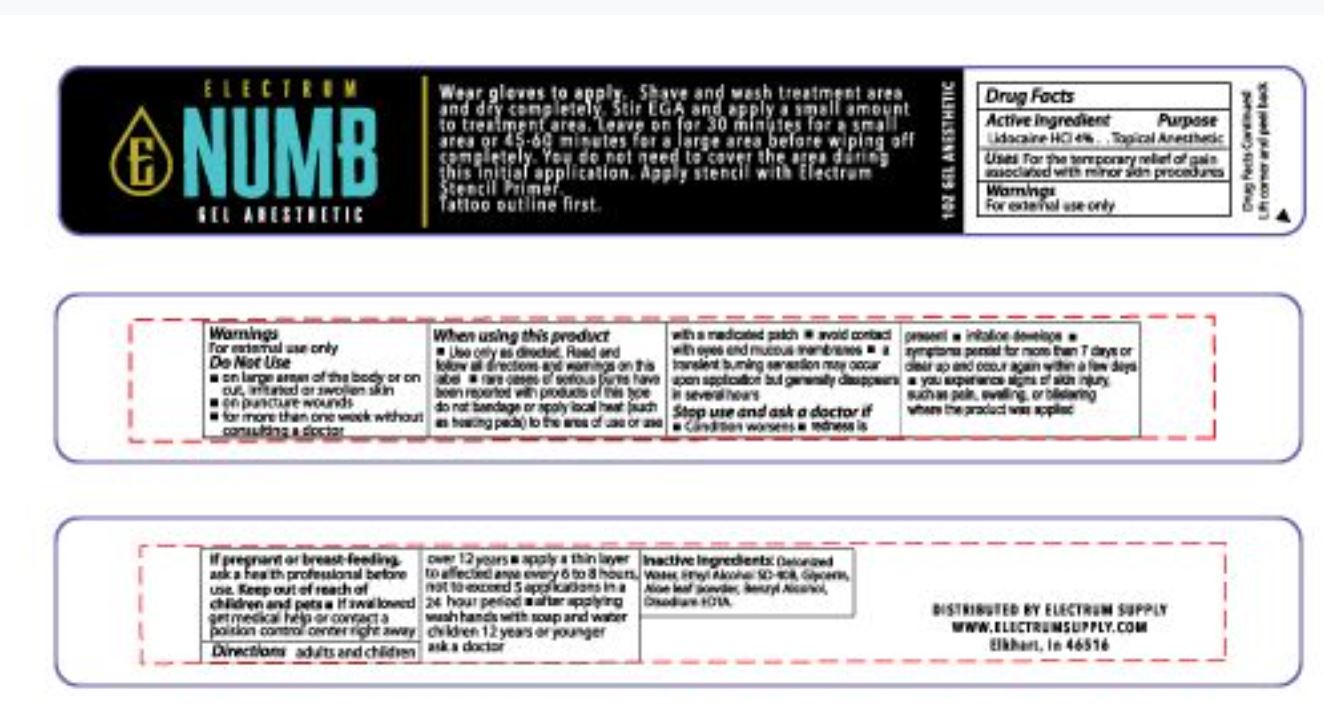 DRUG LABEL: Numb Gel Anesthetic
NDC: 76348-595 | Form: GEL
Manufacturer: RENU LABORATORIES, INC.
Category: otc | Type: HUMAN OTC DRUG LABEL
Date: 20220117

ACTIVE INGREDIENTS: LIDOCAINE HYDROCHLORIDE 1.12 g/28 g
INACTIVE INGREDIENTS: GLYCERIN; EDETATE DISODIUM ANHYDROUS; ALOE VERA LEAF; BENZYL ALCOHOL; WATER; ALCOHOL

NUMB Gel Anesthetic

ACTIVE INGREDIENT

Lidocaine HCl 4%

PURPOSE

Topical anesthetic

INDICATIONS AND USAGE

Uses: For temporary relief of pain associated with minor skin procedures

WARNINGS

For External Use only.

When using this product, do not use in or near the eyes • do not use in large quantities, particularly over raw surfaces or blistered areas. • do not use on puncture wounds • for more than one week without consulting a doctor

Stop Use and ask a doctor if:

- allergic reaction occurs
- condition worsens or does not improve within 7 days
- symptoms clear up and return within a few days
- redness, irritation, swelling, pain or other symptoms begin or increase

Keep out of reach of children. If swallowed, get medical help or contact a Poison Control Center right away.

DOSAGE AND ADMINISTRATION

Directions: adults and children 2 years and older: apply to the affected area up to 3 to 4 times a day

children under 2 years - ask a doctor

INACTIVE INGREDIENT

Inactive Ingredients: Aloe Barbadensis Leaf Powder, Benzyl Alcohol, Deionized Water, Disodium EDTA, Ethyl Alcohol SD 40B, Glycerin

OTHER SAFETY INFORMATION

Store at 20 - 25 C (68 - 77 degrees F)

Questions? 574-975-3632

PREGNANCY OR BREAST FEEDING

If pregnant or breast-feeding, ask a health professional before use.

JAR LABEL AND BOX ART